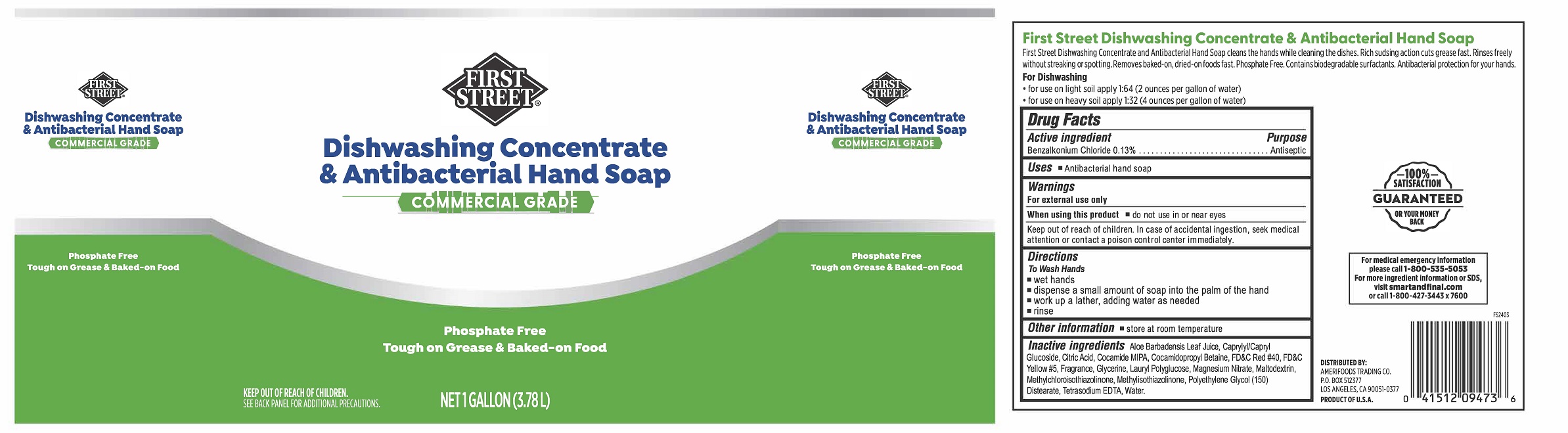 DRUG LABEL: First Street Dishwashing Concentrate and  Antibacterial Hand
NDC: 61504-552 | Form: SOAP
Manufacturer: Amerifoods Trading Company
Category: otc | Type: HUMAN OTC DRUG LABEL
Date: 20251106

ACTIVE INGREDIENTS: BENZALKONIUM CHLORIDE 13 mg/1 mL
INACTIVE INGREDIENTS: ALOE VERA LEAF; CAPRYLYL GLUCOSIDE; ANHYDROUS CITRIC ACID; COCO MONOISOPROPANOLAMIDE; COCAMIDOPROPYL BETAINE; FD&C RED NO. 40; FD&C YELLOW NO. 5; GLYCERIN; LAURYL GLUCOSIDE; MAGNESIUM NITRATE; MALTODEXTRIN; METHYLCHLOROISOTHIAZOLINONE; METHYLISOTHIAZOLINONE; PEG-150 DISTEARATE; EDETATE SODIUM; WATER

First Street Dishwashing Concentrate & Antibacterial Hand Soap

Active ingredient

Benzalkonium Chloride 0.13%

Purpose

Antibacterial

Uses

- Antibacterial Hand Soap

Warnings

For external use only

When using this product

- do not use in or near eyes

Keep out of reach of children. In case of accidental ingestion, seek medical
attention or contact a poison control center immediately.

Directions

• wet hands
• dispense a smalll amout of soap in the palm of the hand

- work up a lather, adding water as needed
- rinse

Other information

• store at room temperature

Inactive ingredients:

Aloe Barbadensis Leaf Juice, Caprylyl/Capryl Glucoside, Citric Acid, Cocamide MIPA, Cocamidopropyl Betaine, FD&C Red #40, FD&C Yellow #5, Fragrance, Glycerine, Lauryl Polyglucose, Magnesium Nitrate, Maltodextrin, Methylchloroisothiazolinone, Methylisothiazolinone, Polyethylene Glycol (150) Distearate, Tetrasodium EDTA, Water.